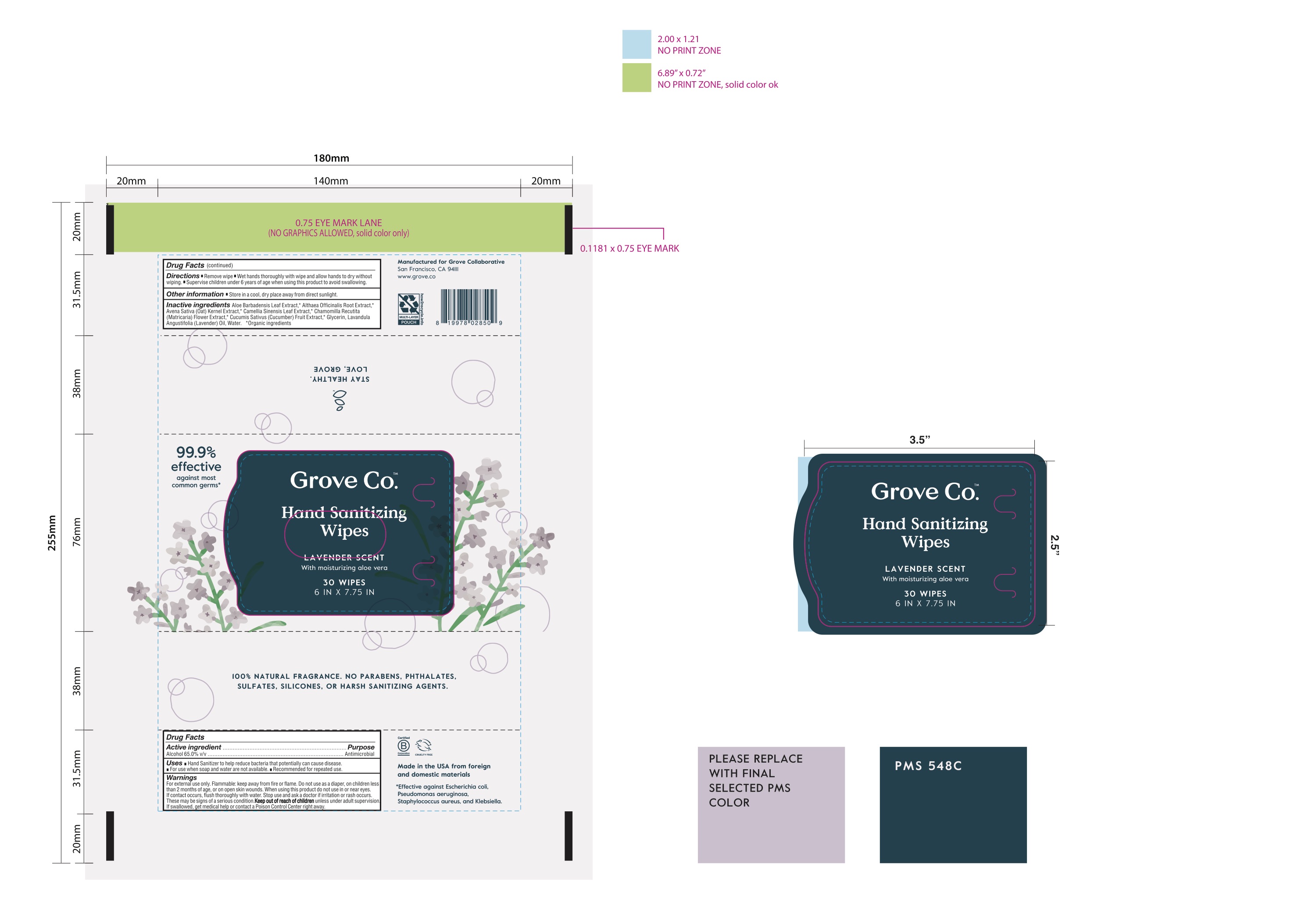 DRUG LABEL: Hand Sanitizing Wipes
NDC: 73315-0717 | Form: CLOTH
Manufacturer: Grove Collaborative
Category: otc | Type: HUMAN OTC DRUG LABEL
Date: 20201223

ACTIVE INGREDIENTS: ALCOHOL 65 mL/100 mL
INACTIVE INGREDIENTS: ALOE VERA LEAF; CHAMOMILE; OAT; LAVENDER OIL; GLYCERIN; WATER; ALTHAEA OFFICINALIS ROOT; GREEN TEA LEAF; CUCUMBER

Active Ingredient(s)

Ethyl Alcohol 65% v/v. Purpose: Antimicrobial

Purpose

Antimicrobial

Use

Hand Sanitizer to help reduce bacteria that potentially can cause disease. For use when water and soap are not available. Recommended for repeated use.

Store in a cool, dry place away from direct sunlight.

Warnings

For external use only. Flammable, keep away from fire or flame

Do not use as a diaper, on children less than 2 months of age, or on open skin wounds. When using this product do not use in or near eyes. If contact occurs, flush thoroughly with water.

When using this product do not use in or near eyes. If contact occurs, flush thoroughly with water.

Stop use and ask a doctor if irritation or rash occurs. These may be signs of a serious condition.

Keep out of reach of children unless under adult supervision. If swallowed, get medical help or contact a Poison Control Center right away.

Directions

- Remove wipe
- Wet hands thoroughly with wipe and allow hands to dry without wiping
- Supervise children under 6 years of age when using this product to avoid swallowing.

Inactive ingredients

Aloe Barbadensis Leaf Extract,* Althaea Officinalis Root Extract,* Avena Sativa (Oat) Kernel Extract,* Camellia Sinensis Leaf Extract,* Chammomilla Recutita (Matricaria) Flower Extract,* Cucumis Sativus (Cucumber) Fruit Extract,* Glycerin, Lavandula Angustifolia(Lavender)Oil,Water.

*Organic ingredients

RECENT MAJOR CHANGES

Indications and Usage: Hand Sanitizer to help reduce bacteria that potentially can cause disease. Store in a cool, dry place away from direct sunlight.

Dosage and Administration: Supervise children under 6 years of age when using this product to avoid swallowing.

Modified lanuage to include 99.9% effect against most common germs

Clarified list of germs this wipe is effective against (Escherichia coli, Pseudomonas aeruginosa, Staphylococcus aureus, and Klebsiella and more")

Package Label - Principal Display Panel

30 wipes

6i IN X 7.75 IN